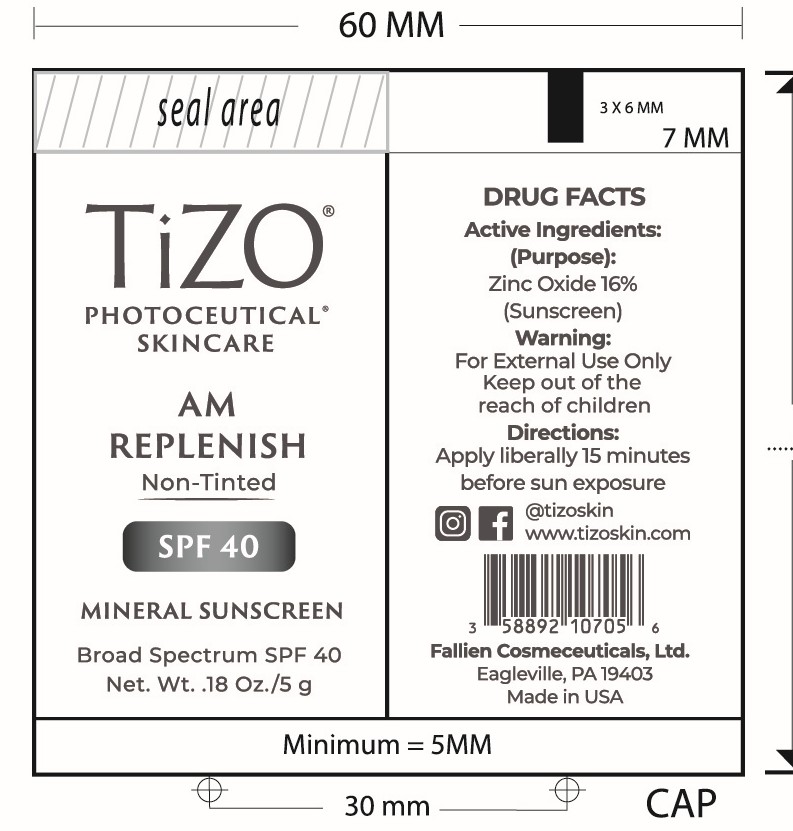 DRUG LABEL: TiZO Photoceutical AM Replenish Non-Tinted
NDC: 58892-107 | Form: CREAM
Manufacturer: Fallien Cosmeceuticals, LTD
Category: otc | Type: HUMAN OTC DRUG LABEL
Date: 20250128

ACTIVE INGREDIENTS: ZINC OXIDE 160 mg/1 g
INACTIVE INGREDIENTS: DIMETHICONE/VINYL DIMETHICONE CROSSPOLYMER (SOFT PARTICLE); CAPRYLIC/CAPRIC TRIGLYCERIDE; CERAMIDE 3; CYCLOHEXASILOXANE; CYCLOPENTASILOXANE; DIMETHICONE CROSSPOLYMER; DIMETHICONOL (2000 CST); HYDROGEN DIMETHICONE (20 CST); VINYL DIMETHICONE/METHICONE SILSESQUIOXANE CROSSPOLYMER; PEG-10 DIMETHICONE (600 CST); POLYHYDROXYSTEARIC ACID (2300 MW); DIMETHICONE; ALPHA-TOCOPHEROL ACETATE; TETRAHEXYLDECYL ASCORBATE

Active Ingredients:

Zinc Oxide 16%

(Purpose)

Sunscreen

Directions:

Apply liberally 15 minutes before sun expsure.

Warning:

For external use only.

Warning and Directions:

For external use only. Apply liberally 15 minutes before sun exposure.

INACTIVE INGREDIENT

Capric/Caprylic Triglyceride, Ceramide 3, Cyclohexasiloxane, Cyclopentasiloxane, Dimethicone, Dimethicone Crosspolymer, Dimethicone/Vinyl Dimethicone Crosspolymer, Dimethiconol, Hydrogen Dimethicone, PEG-10 Dimethicone, Polyhydroxystearic Acid, Tetrahexyldecyl Ascorbate, Tocopheryl Acetate, Vinyl Dimethicone/Methicone Silsesquioxane Crosspolymer

Warning:

Kepp out of the reach of children.